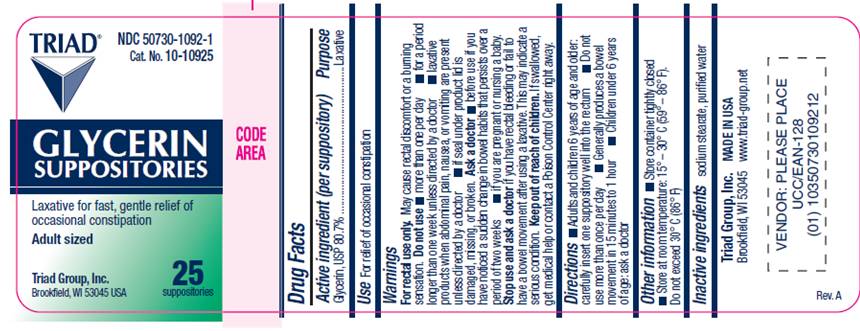 DRUG LABEL: Glycerin
NDC: 50730-1092 | Form: SUPPOSITORY
Manufacturer: H and P Industries, Inc. dba Triad Group
Category: otc | Type: HUMAN OTC DRUG LABEL
Date: 20091120

ACTIVE INGREDIENTS: glycerin 1.614 g/1 1
INACTIVE INGREDIENTS: sodium stearate; water

DRUG FACTS

ACTIVE INGREDIENT

Glycerin, USP 80.7%

PURPOSE

Laxative

USE

For relief of occasional constipation

WARNINGS

For rectal use only. May cause rectal discomfort or a burning sensation.

Do not use

- more than one per day
- for a period of longer than one week unless directed by a doctor
- laxative products when abdominal pain, nausea, or vominting are present unless directed by a doctor
- if seal under product lid is damaged, missing or broken.

Ask a doctor before use

- if you have noticed a sudden change in bowel habits that persist over a period of two weeks
- if you are pregnant or nursing a baby

Keep out of reach of children

If swallowed, get medical help or contact a Poison Control Center right away.

DIRECTIONS

- Adults and children 6 years of age and older: carefully insert one suppository well into the rectum
- Do not use more than once per day
- Generally produces a bowel movement in 15 minutes to 1 hour
- Children under 6 years of age: ask a doctor.

OTHER INFORMATION

- Store container tightly closed
- Store at room temperature: 15°- 30° C (59° - 86° F). Do not exceed 30° C (86° F).

INACTIVE INGREDIENTS

sodium stearate, water

PACKAGE LABEL

TRIAD®
NDC 50730-1092-1
Cat. No. 10-10925
GLYCERIN
SUPPOSITORIES
Laxative for fast, gentle relief of occasional constipation
Adult sized

Triad Group Inc.
Brookfield, WI 53045 USA

25
suppositories